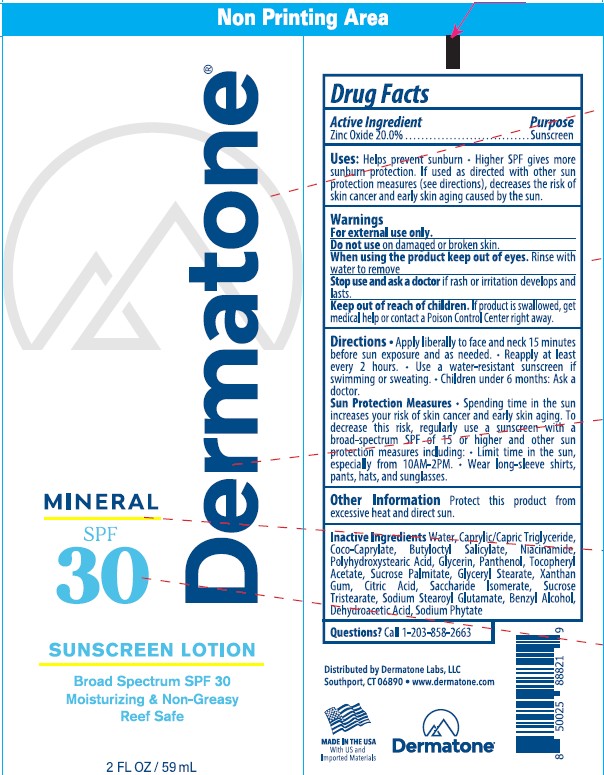 DRUG LABEL: Dermatone Mineral SPF 30
NDC: 54414-030 | Form: LOTION
Manufacturer: Dermatone Labs LLC
Category: otc | Type: HUMAN OTC DRUG LABEL
Date: 20260218

ACTIVE INGREDIENTS: ZINC OXIDE 20 g/100 mL
INACTIVE INGREDIENTS: CAPRYLIC/CAPRIC TRIGLYCERIDE; COCO-CAPRYLATE; BUTYLOCTYL SALICYLATE; NIACINAMIDE; POLYHYDROXYSTEARIC ACID (2300 MW); GLYCERIN; PANTHENOL; .ALPHA.-TOCOPHEROL ACETATE; SUCROSE PALMITATE; GLYCERYL STEARATE; XANTHAN GUM; CITRIC ACID; SACCHARIDE ISOMERATE; WATER; SUCROSE TRISTEARATE; SODIUM STEAROYL GLUTAMATE; BENZYL ALCOHOL; DEHYDROACETIC ACID; SODIUM PHYTATE

Dermatone Mineral SPF 30 Sunscreen Lotion

Active ingredients Purpose

Zinc Oxide 20% Sunscreen

Uses

• Helps prevent sunburn, higher SPF gives more sunburn protection

• if used as directed with other sun protection measures (see Directions),

decreases the risk of skin cancer and early skin aging caused by the sun

WARNINGS

For external use only.

When using this product:

Stop use and ask a doctor ifrash occurs.

Keep out of reach of children.If swallowed, get medical help or contact a Poison Control Center right away

Inactive Ingredeints

WATER
CAPRYLIC/CAPRIC TRIGLYCERIDE
COCO-CAPRYLATE
BUTYLOCTYL SALICYLATE
NIACINAMIDE
POLYHYDROXYSTEARIC ACID
GLYCERIN
PANTHENOL
.ALPHA.-TOCOPHEROL ACETATE
SUCROSE PALMITATE
XANTHAN GUM
CITRIC ACID
SACCHARIDE ISOMERATE
SUCROSE TRISTEARATE
SODIUM STEAROYL GLUTAMATE
BENZYL ALCOHOL
DEHYDROACETIC ACID
SODIUM PHYTATE

DIRECTIONS

• Apply liberally 15 minutes before sun exposure.

• Reapply at least every 2 hours

٠apply to all areas of the skin exposed to the sun.
٠Reapply as needed or after towel drying, swimming, or sweating.

• Sun Protection Measures. Spending tme in the sun increases your risk of skin cancer and early skin aging. To decrease this risk, regularly use a sunscreen with a broad spectrum SPF of 15 or higher and other sun protection measures including: • limit time in the sun, especially from
10 a.m. - 2. p.m. • wear a long-sleeve shirt, pants, hats, and sunglasses.
• children under 6 months: Ask a doctor.